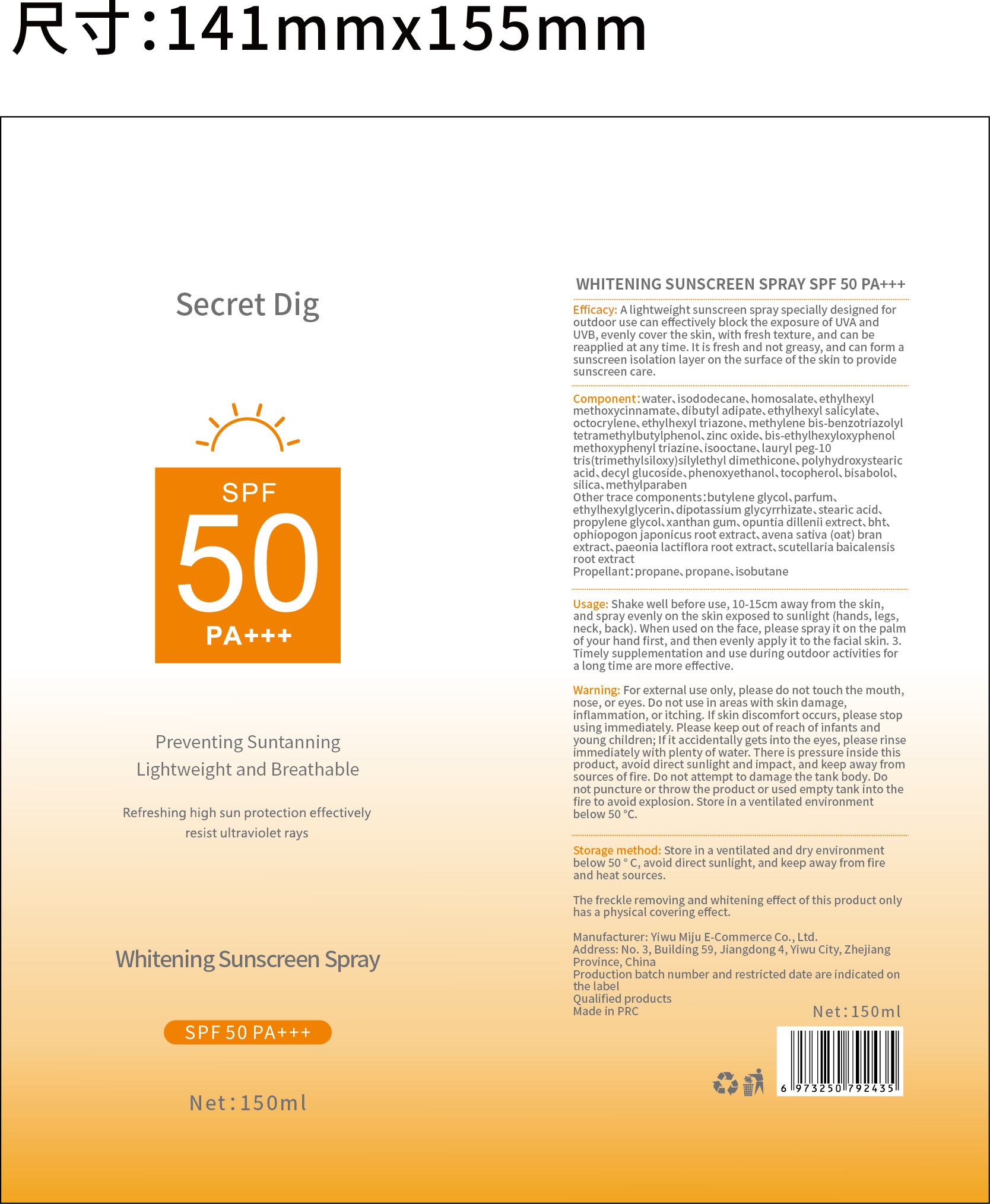 DRUG LABEL: Secret Dig
NDC: 84462-456 | Form: AEROSOL, SPRAY
Manufacturer: Yiwu Mijue electronic Commerce Co., LTD
Category: otc | Type: HUMAN OTC DRUG LABEL
Date: 20240626

ACTIVE INGREDIENTS: HOMOSALATE 36 g/100 g; OCTISALATE 36 g/100 g; OCTINOXATE 20 g/100 g
INACTIVE INGREDIENTS: DECYL GLUCOSIDE; BISOCTRIZOLE; WATER; DEHYDROXANTHAN GUM; N-SALICYLOYLGLYCINE; BEMOTRIZINOL; ETHYLHEXYL TRIAZONE; 2-PHENYLPROPANAL PROPYLENE GLYCOL ACETAL; OCTOCRYLENE; ZINC OXIDE; STEARIC ACID

DOSAGE AND ADMINISTRATION

Store in a ventilated and dry environmen below 50 °c, avoid direct sunlight, and keep away from fire and heat sources.

Net:150ml

ACTIVE INGREDIENT

ETHYLHEXYL METHOXYCINNAMATE,HOMOSALATE,ETHYLHEXYL SALICYLATE,OCTOCRYLENE,ETHYLHEXYL TRIAZONE,BIS-ETHYLHEXYLOXYPHENOL,METHOXYPHENYL TRIAZINE,ZINC OXIDE,SILICA,STEARIC ACID,METHYLENE BIS-BENZOTRIAZOLYL

INACTIVE INGREDIENT

WATER 45%
METHYLPARABEN 5%
BHT 2%
ISODODECANE 2%
ISOOCTANE 2%
DIBUTYL ADIPATE 1%
LAURYL PEG-10 TRIS(TRIMETHYLSILOXY)SILYLETHYL DIMETHICONE 1%
TOCOPHEROL 1%
POLYHYDROXYSTEARIC ACID 1%
BISABOLOL 1%
TOCOPHEROL 1%
PARFUM 1%
DIPOTASSIUM GLYCYRRHIZATE 1%
PHENOXYETHANOL 1%
ETHYLHEXYLGLYCERIN 1%
BUTYLENE GLYCOL 1%
OPUNTIA DILLENII EXTRECT 1%
AVENA SATIVA (OAT) BRAN EXTRACT 0.5%
OPHIOPOGON JAPONICUS ROOT EXTRACT 0.5%
PAEONIA LACTIFLORA ROOT EXTRACT 0.5%
SCUTELLARIA BAICALENSIS ROOT EXTRACT 0.5%

PURPOSE

A lightweight sunscreen spray specially designed foroutdoor use can effectively block the exposure of UVA andUVB,evenly cover the skin, with fresh texture, and can breapplied at any time.lt is fresh and not greasy, and can formsunscreen isolation layer on the surface of the skin to providesunscreen care.

RECENT MAJOR CHANGES

Store in a ventilated and dry environmen below 50 °c, avoid direct sunlight, and keep away from fire and heat sources.

Net:150ml

KEEP OUT OF REACH OF CHILDREN

Please keep out of reach of infants and young children

INDICATIONS AND USAGE

A lightweight sunscreen spray specially designed for outdoor use can effectively block the exposure of UVA and UVB

Usage:Shake well before use,10-15cm away from the skin and spray evenly on the skin exposed to sunlight(hands,legs,neck,back)

WARNINGS

Warning:For external use only,please do not ch e mouh,nose or eyes,do not use in areas with skin damage inflammation or itching